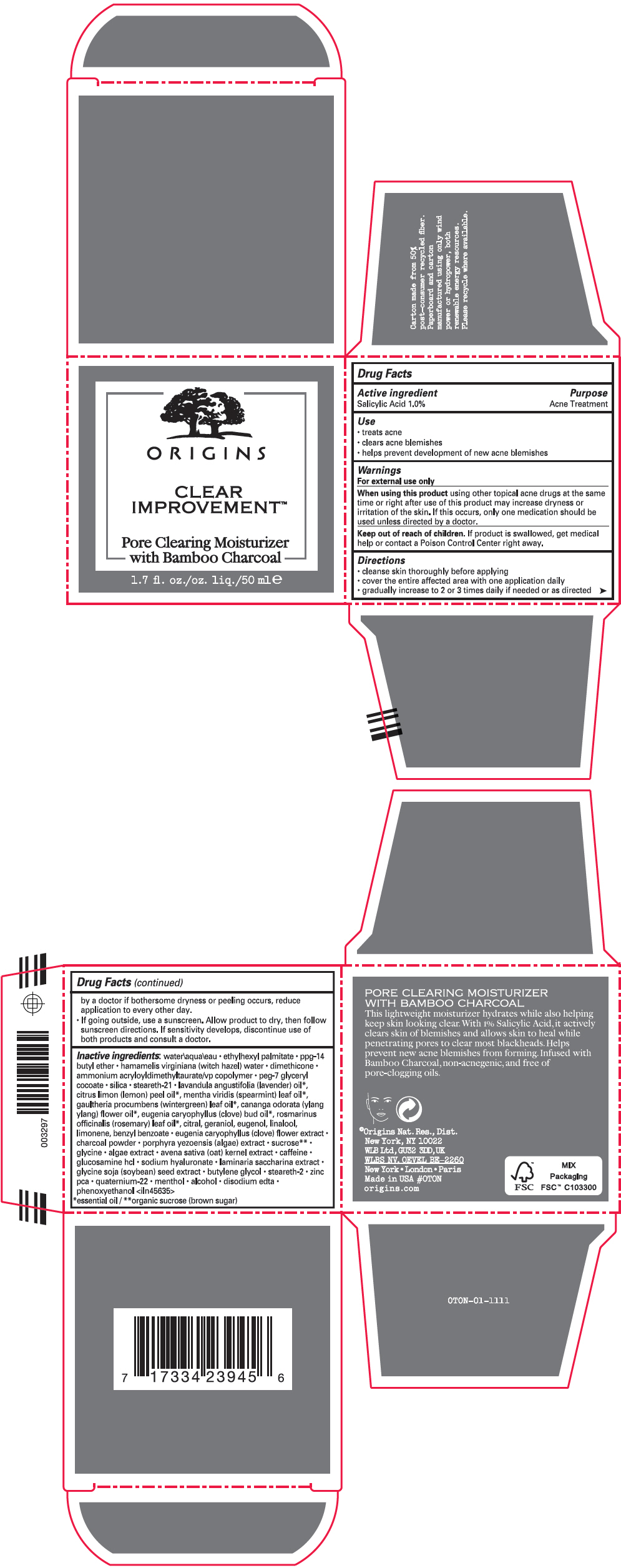 DRUG LABEL: CLEAR IMPROVEMENT PORE CLEARING MOISTURIZER
NDC: 59427-015 | Form: LOTION
Manufacturer: ORIGINS NATURAL RESOURCES INC.
Category: otc | Type: HUMAN OTC DRUG LABEL
Date: 20230912

ACTIVE INGREDIENTS: SALICYLIC ACID 10 mg/1 mL
INACTIVE INGREDIENTS: STEARETH-21; LAVENDER OIL; LEMON OIL, COLD PRESSED; SPEARMINT OIL; METHYL SALICYLATE; YLANG-YLANG OIL; CLOVE OIL; ROSEMARY OIL; CITRAL; GERANIOL; EUGENOL; LINALOOL, (+/-)-; LIMONENE, (+)-; BENZYL BENZOATE; CLOVE; ACTIVATED CHARCOAL; PHYMATOLITHON CALCAREUM; SUCROSE; GLYCINE; OAT; CAFFEINE; GLUCOSAMINE HYDROCHLORIDE; HYALURONATE SODIUM; SACCHARINA LATISSIMA; SOYBEAN; BUTYLENE GLYCOL; STEARETH-2; ZINC PIDOLATE; QUATERNIUM-22; MENTHOL, UNSPECIFIED FORM; ALCOHOL; EDETATE DISODIUM; PHENOXYETHANOL; WITCH HAZEL; WATER; ETHYLHEXYL PALMITATE; PPG-14 BUTYL ETHER; DIMETHICONE; AMMONIUM ACRYLOYLDIMETHYLTAURATE/VP COPOLYMER; PEG-7 GLYCERYL COCOATE; SILICON DIOXIDE

CLEAR IMPROVEMENT™ PORE CLEARING MOISTURIZER
ACNE

Drug Facts

Active ingredient

Salicylic Acid 1.0%

Purpose

Acne Treatment

Use

- treats acne
- clears acne blemishes
- helps prevent development of new acne blemishes

Warnings

For external use only

When using this product using other topical acne drugs at the same time or right after use of this product may increase dryness or irritation of the skin. If this occurs, only one medication should be used unless directed by a doctor.

Keep out of reach of children. If product is swallowed, get medical help or contact a Poison Control Center right away.

Directions

- cleanse skin thoroughly before applying
- cover the entire affected area with one application daily
- gradually increase to 2 or 3 times daily if needed or as directed by a doctor if bothersome dryness or peeling occurs, reduce application to every other day.
- If going outside, use a sunscreen. Allow product to dry, then follow sunscreen directions. If sensitivity develops, discontinue use of both products and consult a doctor.

Inactive ingredients

water\aqua\eau • ethylhexyl palmitate • ppg-14 butyl ether • hamamelis virginiana (witch hazel) water • dimethicone • ammonium acryloyldimethyltaurate/vp copolymer • peg-7 glyceryl cocoate • silica • steareth-21 • lavandula angustifolia (lavender) oil [essential oil] , citrus limon (lemon) peel oil , mentha viridis (spearmint) leaf oil , gaultheria procumbens (wintergreen) leaf oil , cananga odorata (ylang ylang) flower oil , eugenia caryophyllus (clove) bud oil , rosmarinus officinalis (rosemary) leaf oil , citral, geraniol, eugenol, linalool, limonene, benzyl benzoate • eugenia caryophyllus (clove) flower extract • charcoal powder • porphyra yezoensis (algae) extract • sucrose [organic sucrose (brown sugar)] • glycine • algae extract • avena sativa (oat) kernel extract • caffeine • glucosamine hcl • sodium hyaluronate • laminaria saccharina extract • glycine soja (soybean) seed extract • butylene glycol • steareth-2 • zinc pca • quaternium-22 • menthol • alcohol • disodium edta • phenoxyethanol <iln45635>

PRINCIPAL DISPLAY PANEL - 50 ml Jar Carton

ORIGINS

CLEAR
IMPROVEMENT™

Pore Clearing Moisturizer
with Bamboo Charcoal

1.7 fl. oz./oz. liq./50 mle